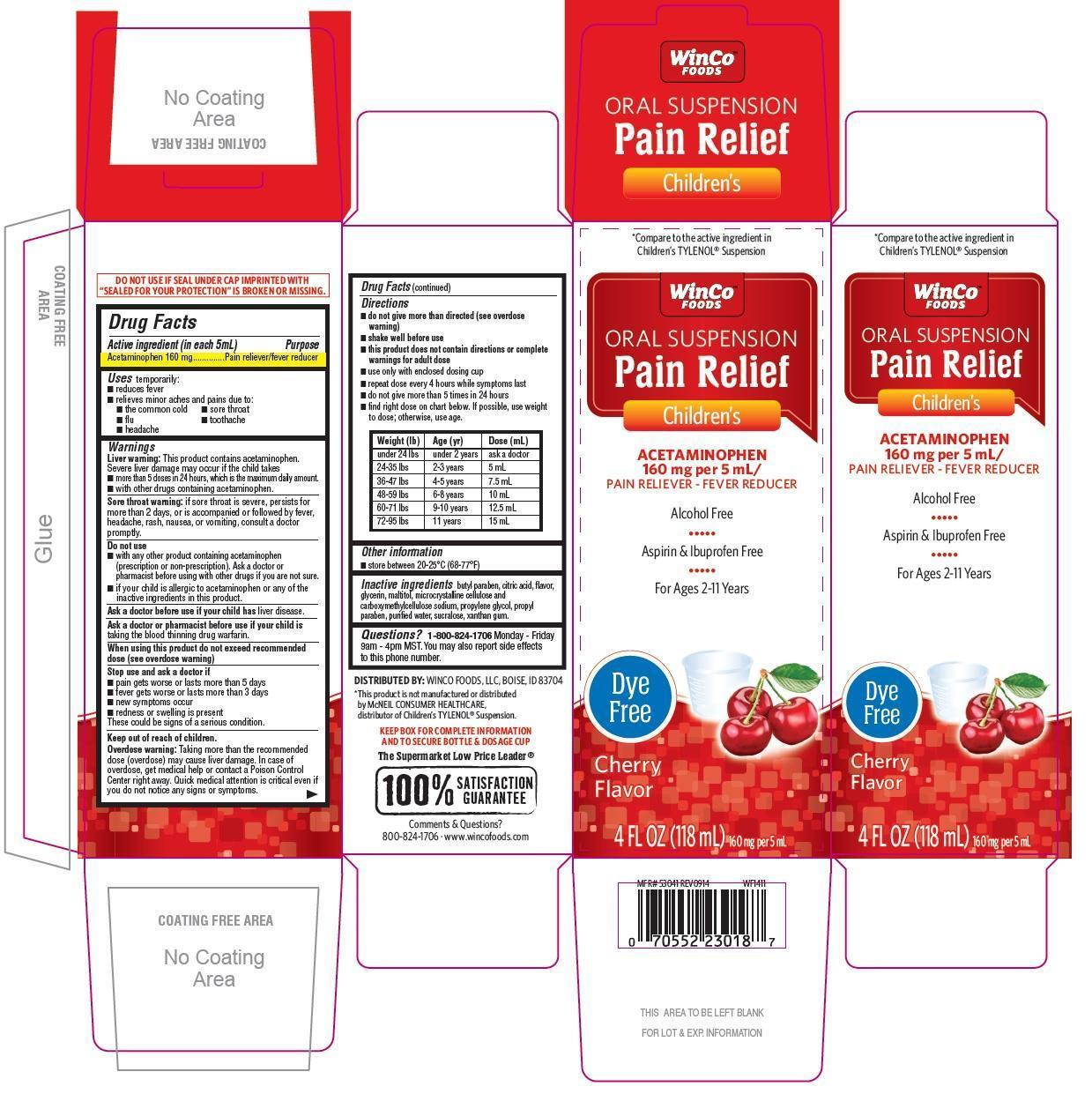 DRUG LABEL: Childrens Pain Relief Dye-Free
NDC: 67091-120 | Form: SUSPENSION
Manufacturer: WinCo Foods, LLC
Category: otc | Type: HUMAN OTC DRUG LABEL
Date: 20191209

ACTIVE INGREDIENTS: ACETAMINOPHEN 160 mg/5 mL
INACTIVE INGREDIENTS: ANHYDROUS CITRIC ACID; BUTYLPARABEN; GLYCERIN; MALTITOL; CELLULOSE, MICROCRYSTALLINE; CARBOXYMETHYLCELLULOSE SODIUM; PROPYLPARABEN; WATER; SUCRALOSE; XANTHAN GUM; PROPYLENE GLYCOL

Childrens Pain Relief Oral Suspension Dye-Free

Active ingredients (in each 5 mL teaspoon)

Acetaminophen 160 mg

Purpose

Pain reliever/fever reducer

Uses

- temporarily reduces fever
- relieves minor Aches and pains due to:
- the common cold
- sore throat
- flu
- toothache
- headache

Warnings

- Liver warning: This product contains acetaminophen. Severe liver damage may occur if the child takes:
- more than 5 doses in 24 hours, which is maximum daily amount
- with other drugs containing acetaminophen
- Sore throat warning: if sore throat is severe, persists for more than 2 days, or is accompanied or followed by fever, headache, rash, nausea, or vomiting, consult a doctor promptly.

Do not use

- with any other drug containing acetaminophen (prescription or non prescription). Ask a doctor or pharmacist before using with other drugs if you are not sure.
- if your child is allergic to acetaminophen or any of the inactive ingredients in this product.

Ask a doctor before use if your child has

liver disease

Ask a doctor or pharmacist before use if your child is

taking the blood thinning drug warfarin

When using this product

do not exceed recommended dose (see overdose warning)

Stop use and ask a doctor if

- pain gets worse or lasts more than 5 days
- fever gets worse or lasts more than 3 days
- redness or swelling is present
- new symptoms occur
- These could be signs of a serious condition.

Keep out of reach of children.

Overdose warning: Taking more than the recommended dose (overdose) may cause liver damage. In case of overdose, get medical help or contact a poison control center right away. Quick medical attention is critical for adults as well as for children even if you do not notice any signs or symptoms.

Directions

- do not give more than directed (see overdose warning)
- shake well before use
- this product does not contain directions or complete warnings for adult dose
- use only enclosed dosing cup
- repeat dose every 4 hours while symptoms last
- do not give more than 5 times in 24 hours
- find right dose on chart below. If possible, use weight to dose; otherwise, use age.

Weight (lb) | Age (yr) | Dose (mL)
under 24 lbs | under 2 years | ask a doctor
24-35 lbs | 2-3 years | 5 mL
36-47 lbs | 4-5 years | 7.5 mL
48 - 59 lbs | 6-8 years | 10 mL
60 - 71 lbs | 9-10 years | 12.5 mL
72 - 95 lbs | 11 years | 15 mL

Other information

- store between 20-25oC(68-77oF)

Inactive ingredients

citric acid anhydrous, butyl paraben, flavor, glycerin, maltitol, microcrystalline cellulose and carboxymethylcellulose sodium, propylene glycol, propyl paraben, purified water, sucralose, xanthan gum

PDP

*Compare to the active ingredient in Childrens TYLENOL®Suspension

Childrens Pain Relief Oral Suspension

ACETAMINOPHEN 160 mg per 5 mL

PAIN RELIEVER-FEVER REDUCER

Alcohol Free

Aspirin & Ibuprofen Free

For Ages 2-11 Years

Dye-Free

Cherry Flavor

4 FL OZ (118 mL) 160 mg per 5 mL